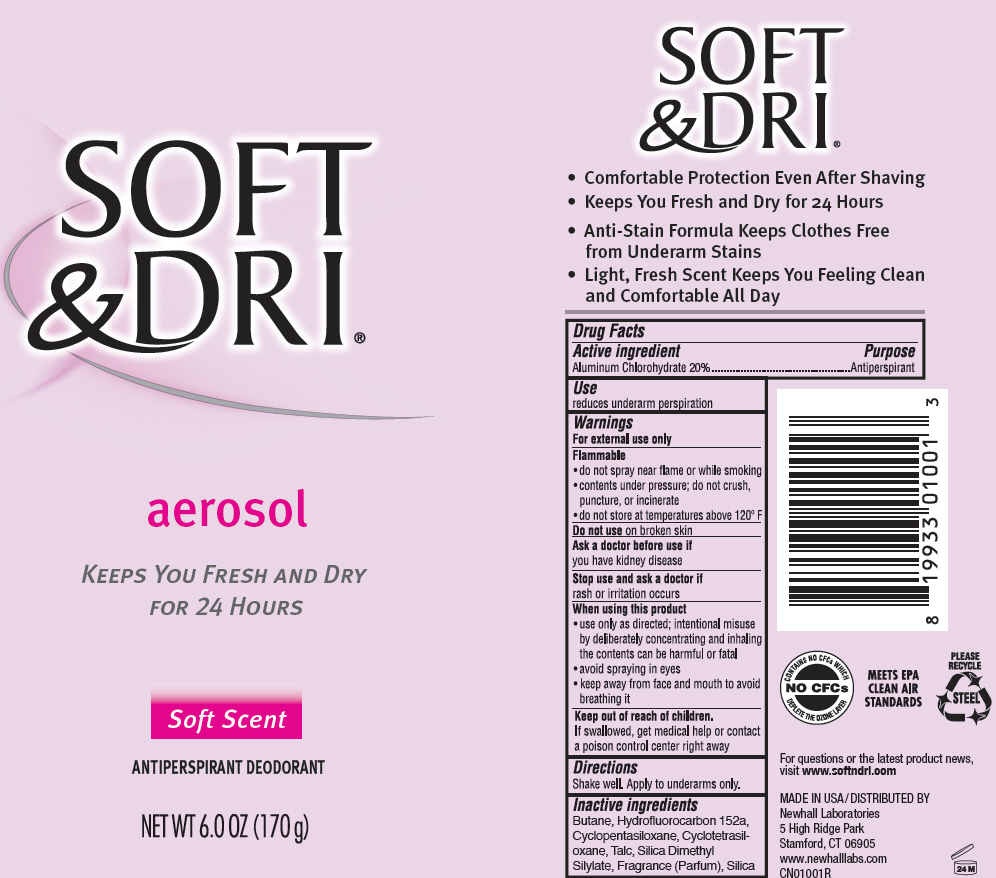 DRUG LABEL: SOFT and DRI Soft Scent
NDC: 31774-1001 | Form: AEROSOL, SPRAY
Manufacturer: Golden Sun Inc DBA Newhall Laboratories
Category: otc | Type: HUMAN OTC DRUG LABEL
Date: 20151106

ACTIVE INGREDIENTS: Aluminum Chlorohydrate 200 mg/1 g
INACTIVE INGREDIENTS: Butane; 1,1-Difluoroethane; Cyclomethicone 5; Cyclomethicone 4; Talc; Silica Dimethyl Silylate; Silicon Dioxide

SOFT & DRI® Aerosol Soft Scent

Drug Facts

Active ingredient

Aluminum Chlorohydrate 20%

Purpose

Antiperspirant

Use

reduces underarm perspiration

Warnings

For external use only

Flammable

- do not spray near flame or while smoking
- contents under pressure; do not crush, puncture, or incinerate
- do not store at temperatures above 120° F

Do not use on broken skin

Ask doctor before use if

you have kidney disease

Stop use and ask a doctor if

rash or irritation occurs

When using this product

- use only as directed; intentional misuse by deliberately concentrating and inhaling the contents can be harmful or fatal
- avoid spraying in eyes
- keep away from face and mouth to avoid breathing it

Keep out of reach of children.

If swallowed, get medical help or contact a poison control center right away

Directions

Shake well. Apply to underarms only.

Inactive ingredients

Butane, Hydrofluorocarbon 152a, Cyclopentasiloxane, Cyclotetrasiloxane, Talc, Silica Dimethyl Silylate, Fragrance (Parfum), Silica

QUESTIONS

For questions or the latest product news, visit www.softndri.com

DISTRIBUTED BY
Newhall Laboratories
5 High Ridge Park
Stamford, CT 06905

PRINCIPAL DISPLAY PANEL - 170 g Can Label

SOFT
&DRI®

aerosol

KEEPS YOU FRESH AND DRY
FOR 24 HOURS

Soft Scent

ANTIPERSPIRANT DEODORANT

NET WT 6.0 OZ (170 g)